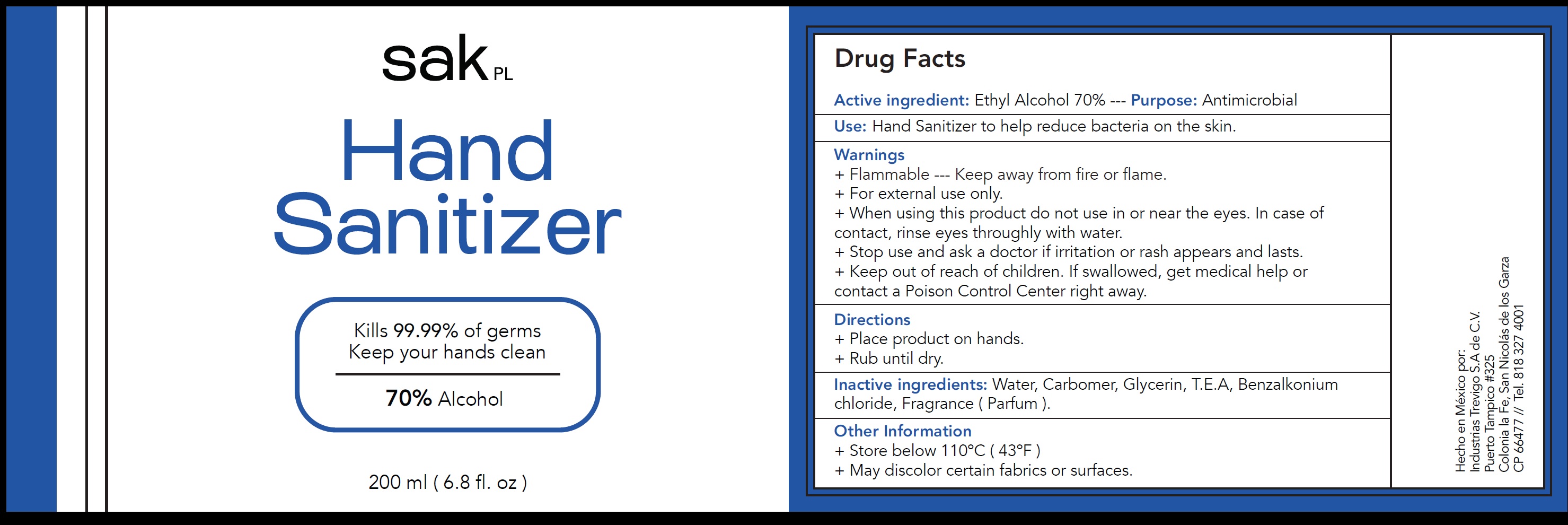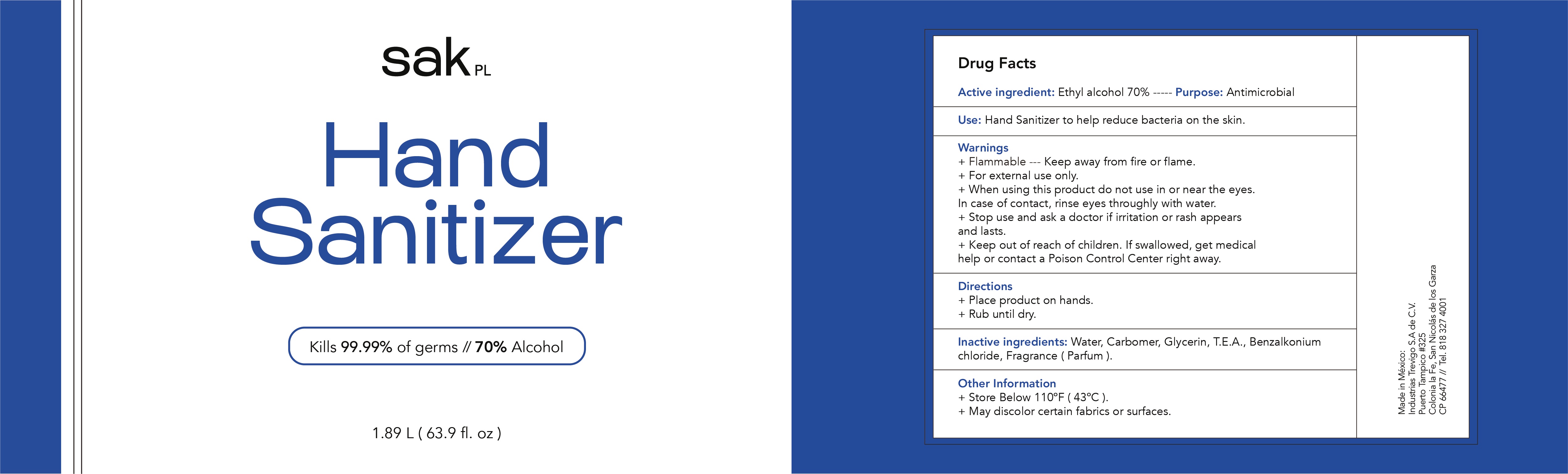 DRUG LABEL: Sak PL Hand Sanitizer 70 Alcohol
NDC: 79409-001 | Form: GEL
Manufacturer: Industrias Trevigo, S.A. de C.V.
Category: otc | Type: HUMAN OTC DRUG LABEL
Date: 20201012

ACTIVE INGREDIENTS: ALCOHOL 0.7 mL/1 mL
INACTIVE INGREDIENTS: WATER; CARBOMER HOMOPOLYMER, UNSPECIFIED TYPE; GLYCERIN; TEA LEAF; BENZALKONIUM CHLORIDE

Sak PL Hand Sanitizer 70% Alcohol

Active ingredient:

Ethyl Alcohol 70%

Purpose:

Antimicrobial

Use:

Hand Sanitizer to help reduce bacteria on the skin.

Warnings

+ Flammable --- Keep away from fire or flame.
+ For external use only.

When using this product

+do not use in or near the eyes. In case of contact, rinse eyes throughly with water.

+Stop use and ask a doctor

if irritation or rash appears and lasts.

Keep out of reach of children.

If swallowed, get medical help or contact a Poison Control Center right away.

Directions

+ Place product on hands.

+ Rub until dry.

Inactive ingredients:

Water, Carbomer, Glycerin, T.E.A, Benzalkonium chloride, Fragrance (Parfum).

Other Information

+ Store below 110ºC (43ºF)
+ May discolor certain fabrics or surfaces.